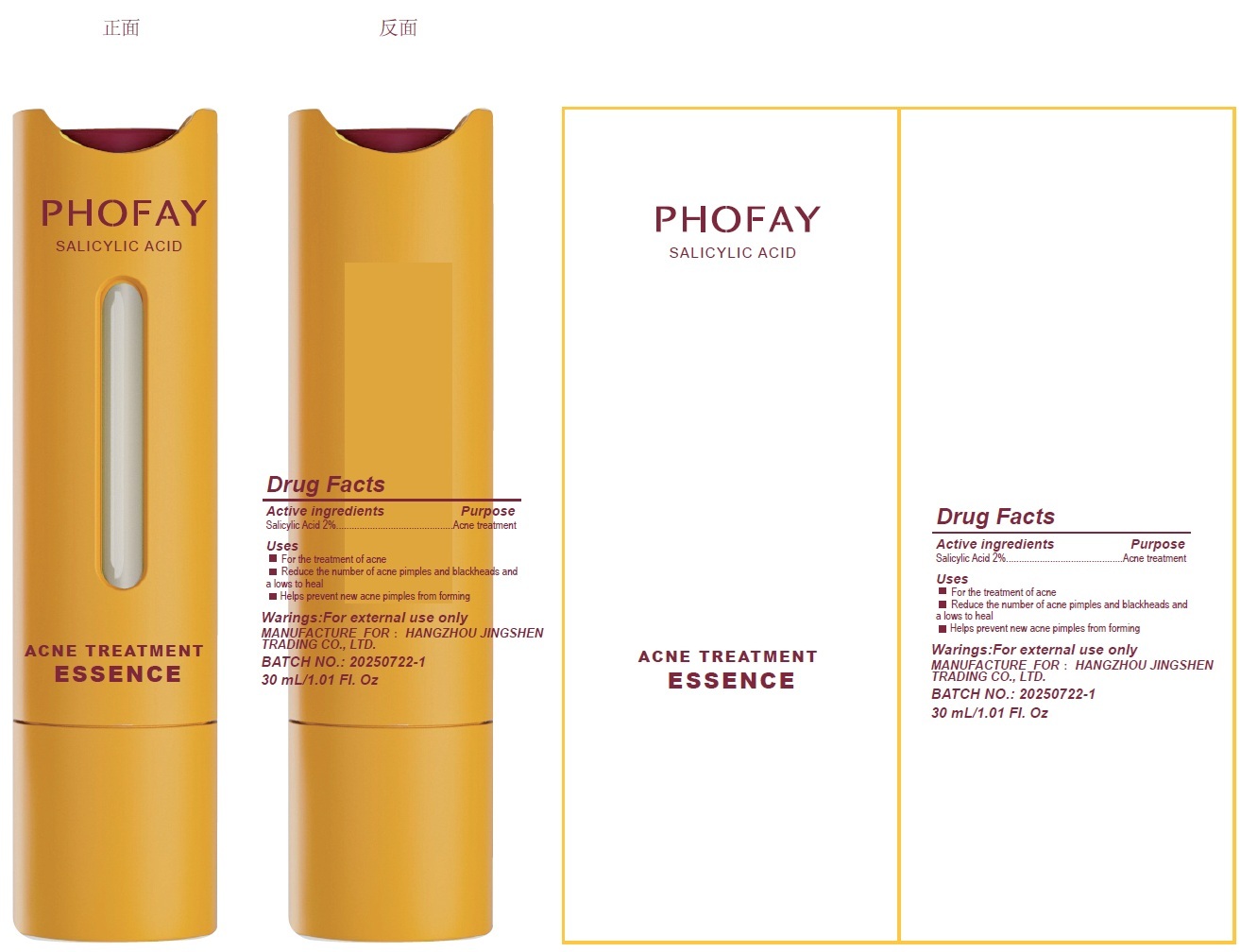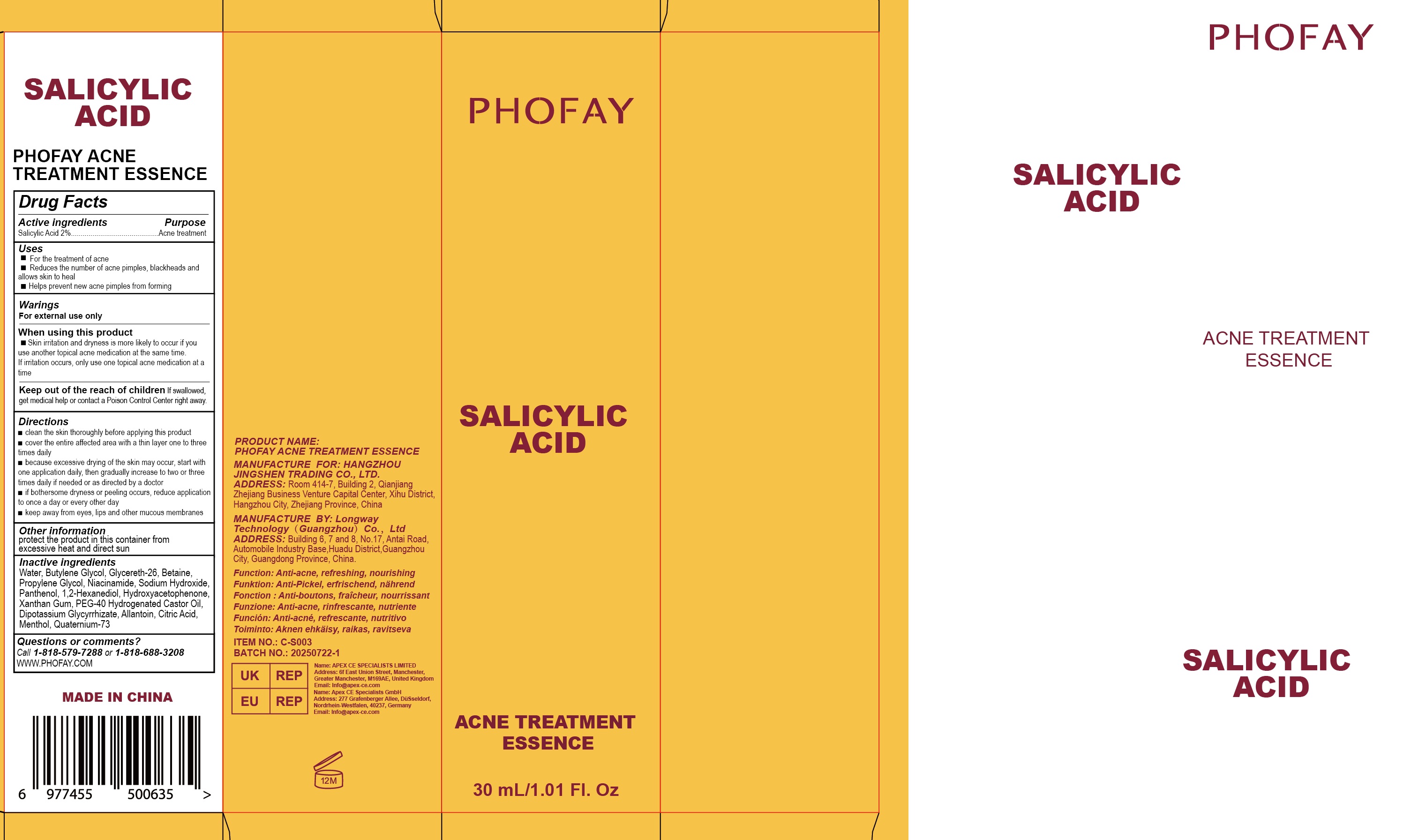 DRUG LABEL: PHOFAY Salicylic Acid Acne Treatment Essence
NDC: 87080-001 | Form: LIQUID
Manufacturer: Hangzhou Jingshen Trading Co., Ltd.
Category: otc | Type: HUMAN OTC DRUG LABEL
Date: 20250904

ACTIVE INGREDIENTS: SALICYLIC ACID 20 mg/1 mL
INACTIVE INGREDIENTS: WATER; BUTYLENE GLYCOL; GLYCERETH-26; BETAINE; PROPYLENE GLYCOL; NIACINAMIDE; SODIUM HYDROXIDE; PANTHENOL; 1,2-HEXANEDIOL; HYDROXYACETOPHENONE; XANTHAN GUM; PEG-40 HYDROGENATED CASTOR OIL; DIPOTASSIUM GLYCYRRHIZATE; ALLANTOIN; CITRIC ACID MONOHYDRATE; MENTHOL; QUATERNIUM-73

PHOFAY Salicylic Acid Acne Treatment Essence

Active ingredients

Salicylic Acid 2%

Purpose

Acne Treatment

Uses

- For the treatment of acne
- Reduce the number of acne pimples and blackheads and allows skin to heal
- Helps prevent new acne pimples from forming

Warnings

For external use only

When using this product

- Skin irritation and dryness is more likely to occur if you use another topical acne medication at the same time. If irritation occurs, only use one topical acne medication at a time

Keep out of the reach of children.

If swallowed, get medical help or contact a Poison Control Center right away.

Directions

- clean the skin thoroughly before applying this product
- cover the entire affected area with a thin layer one to three times daily
- because excessive drying of the skin may occur, start with one application daily, then gradually increase to two or three times daily if needed or as directed by a doctor
- if bothersome dryness or peeling occurs, reduce application to once a day or every other day
- keep away from eyes, lips and other mucus membranes

Other information

protect the product in this container from excessive heat and direct sun

Inactive ingredients

Water, Butylene Glycol, Glycereth-26, Betaine, Propylene Glycol, Niacinamide, sodium Hydroxide, Panthenol, 1,2-Hexanediol, Hydroxyacetophenone, Xanthan Gum, PEG-40 Hydrogenated Castor Oil, Dipotassium Glycyrrhizate, Allantoin, Citric Acid, Menthol, Quaternium-73

Questions or comments?

Call 1-818-579-7288or 1-818-688-3208WWW.PHOFAY.COM